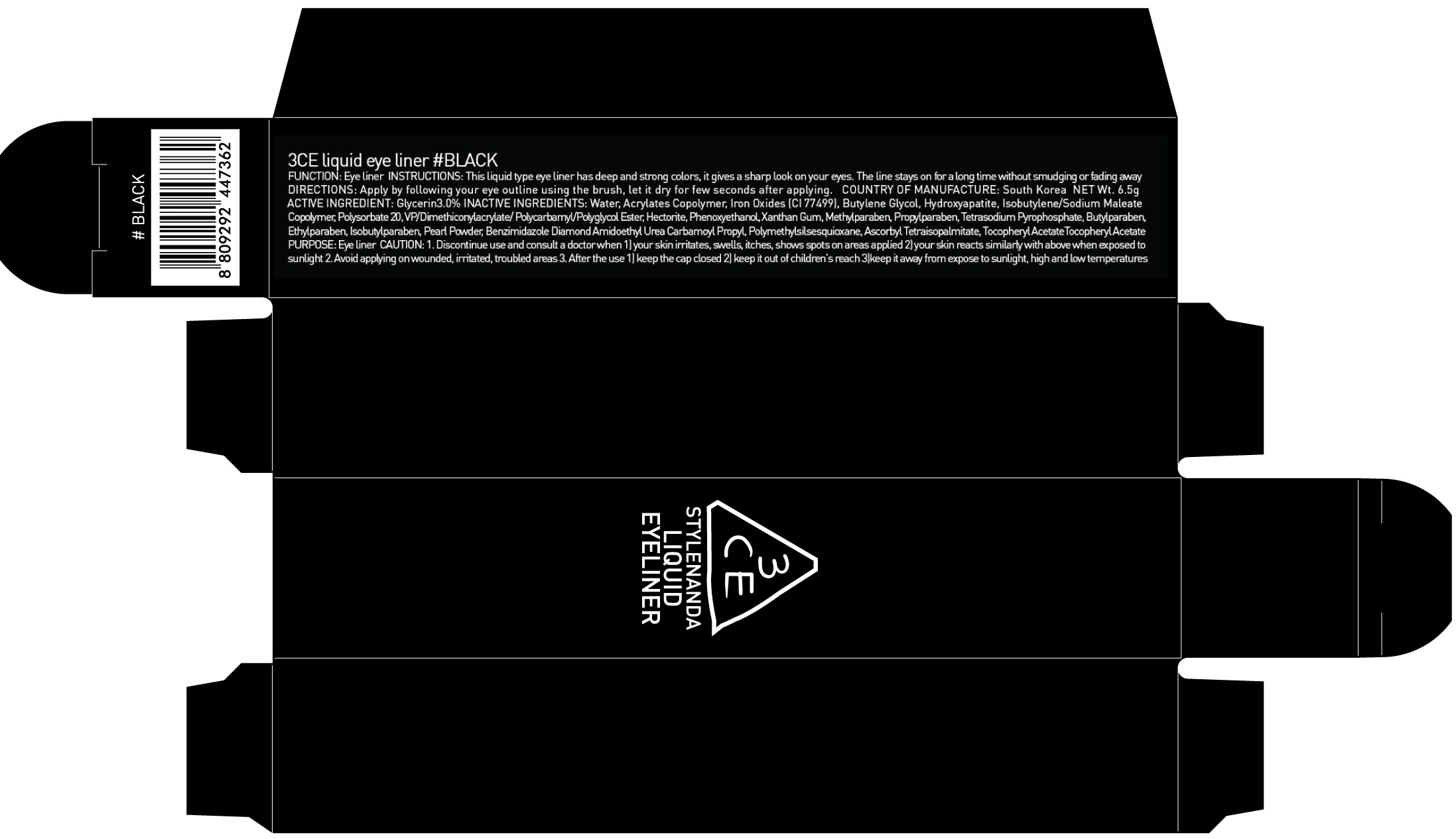 DRUG LABEL: 3CE LIQU ID EYE LINER BLACK
NDC: 60764-044 | Form: LIQUID
Manufacturer: Nanda Co., Ltd
Category: otc | Type: HUMAN OTC DRUG LABEL
Date: 20160930

ACTIVE INGREDIENTS: Glycerin 0.19 g/6.5 g
INACTIVE INGREDIENTS: Water; Butylene Glycol

ACTIVE INGREDIENT

Active Ingredient: Glycerin 3.0%

INACTIVE INGREDIENT

Inactive Ingredients: Water, Acrylates Copolymer, Iron Oxides (CI 77499), Butylene Glycol, Hydroxyapatite, Isobutylene/Sodium Maleate Copolymer, Polysorbate 20, VP/Dimethiconylacrylate/ Polycarbamyl/Polyglycol Ester, Hectorite, Phenoxyethanol, Xanthan Gum, Methylparaben, Propylparaben, Tetrasodium Pyrophosphate, Butylparaben, Ethylparaben, Isobutylparaben, Pearl Powder, Benzimidazole Diamond Amidoethyl Urea Carbamoyl Propyl, Polymethylsilsesquioxane, Ascorbyl Tetraisopalmitate, Tocopheryl AcetateTocopheryl Acetate

PURPOSE

Purpose: Eye Liner

CAUTION

CAUTION: 1. Discontinue use and consult a doctor when - your skin irritates, swells, itches, shows spots on areas applied - your skin reacts similarly with above when exposed to sunlight 2. Avoid applying on wounded, irritated, troubled areas 3. After the use - keep the cap closed - keep it out of children's reach - keep it away from expose to sunlight, high and low temperatures

KEEP OUT OF REACH OF CHILDREN

keep it out of children's reach

INSTRUCTIONS

INSTRUCTIONS: This liquid type eye liner has deep and strong colors, it gives a sharp look on your eyes. The line stays on for a long time without smudging or fading away

Directions

Directions: Apply by following your eye outline using the brush, let it dry for few seconds after applying.